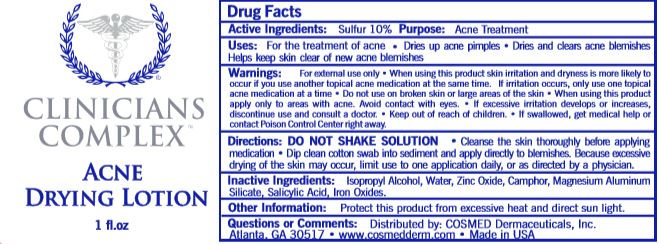 DRUG LABEL: Clinicians Complex
NDC: 61352-001 | Form: LOTION
Manufacturer: Cosmed Dermaceuticals, Inc.
Category: otc | Type: HUMAN OTC DRUG LABEL
Date: 20251111

ACTIVE INGREDIENTS: SULFUR 100 mg/1 g
INACTIVE INGREDIENTS: ISOPROPYL ALCOHOL; WATER; ZINC OXIDE; CAMPHOR (SYNTHETIC); MAGNESIUM ALUMINUM SILICATE; SALICYLIC ACID

Clinicians Complex Acne Drying Lotion

Active Ingredients:

Sulfur 10%

Purpose

Acne Treatment

Uses:

For the treatment of acne • Dries up acne pimples • Dries and clears acne blemishes

Helps keep skin clear of new acne blemishes

Warnings:

For external use only • When using this product skin irritation and dryness is more likely to occur if you use another topical acne medication at the same time. If irritation occurs, only use one topical acne medication at a time • Do not use on broken skin or large areas of the skin • When using this product apply only to areas with acne. Avoid contact with eyes • If excessive irritation develops or increases, discontinue use and consult a doctor • Keep out of reach of children • If swallowed, get medical help or contact Poison Control Center right away.

Keep out of reach of children.

Directions:

DO NOT SHAKE SOLUTION • Cleanse the skin thoroughly before applying medication • Dip clean cotton swab into sediment and apply directly to blemishes. Because excessive drying of the skin may occur, limit use to one application daily, or as directed by a physician.

Inactive Ingredients:

Isopropyl Alcohol, Water, Zinc Oxide, Camphor, Magnesium Aluminum Silicate, Salicylic Acid, Iron Oxides.

Other Information:

Protect this product from excessive heat and direct sun light.

Questions or Comments:

Distibuted by: Cosmed Dermaceuticals, Inc.

Atlanta, GA 30517 • www.cosmedderm.com • Made in USA